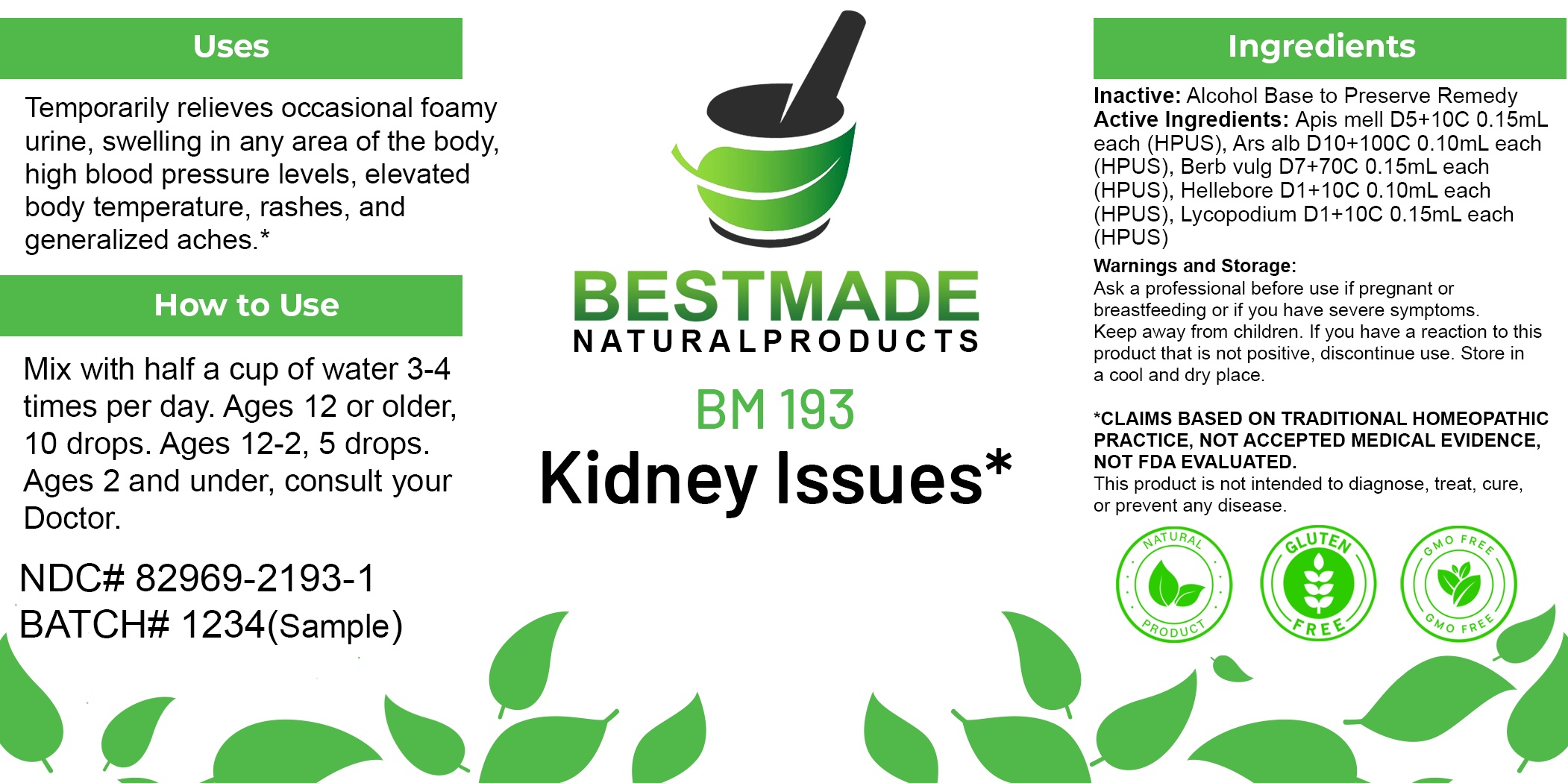 DRUG LABEL: Bestmade Natural Products BM193
NDC: 82969-2193 | Form: LIQUID
Manufacturer: Bestmade Natural Products
Category: homeopathic | Type: HUMAN OTC DRUG LABEL
Date: 20250221

ACTIVE INGREDIENTS: BERBERIS VULGARIS ROOT BARK 30 [hp_C]/30 [hp_C]; HELLEBORUS NIGER ROOT 30 [hp_C]/30 [hp_C]; LYCOPODIUM CLAVATUM SPORE 30 [hp_C]/30 [hp_C]; APIS MELLIFERA 30 [hp_C]/30 [hp_C]; ARSENIC TRIOXIDE 30 [hp_C]/30 [hp_C]
INACTIVE INGREDIENTS: ALCOHOL 30 [hp_C]/30 [hp_C]

BM193

DOSAGE AND ADMINISTRATION

How to Use

Mix with half a cup of water 3-4 times per day. Ages 12 or older, 10 drops. Ages 12-2, 5 drops. Ages 2 and under, consult your Doctor.

Inactive:

Alcohol Base to Preserve Product

ACTIVE INGREDIENT

Active Ingredients: Apis mell D5+10C 0.15mL each (HPUS), Ars alb D10+100C 0.10mL each (HPUS), Berb vulg D7+70C 0.15mL each (HPUS), Hellebore D1+10C 0.10mL each (HPUS), Lycopodium D1+10C 0.15mL each (HPUS)

KEEP OUT OF REACH OF CHILDREN

Warnings and Storage:

Ask a professional before use if pregnant or breastfeeding or if you have severe symptoms.

Keep away from children. If you have a reaction to this product that is not positive, discontinue use. Store in a cool and dry place

*CLAIMS BASED ON TRADITIONAL HOMEOPATHIC PRACTICE, NOT ACCEPTED MEDICAL EVIDENCE NOT FDA EVALUATED.
This product is not intended to diagnose, treat, cure, or prevent any disease.

Warnings and Storage:

Ask a professional before use if pregnant or breastfeeding or if you have severe symptoms.

Keep away from children. If you have a reaction to this product that is not positive, discontinue use. Store in a cool and dry place

*CLAIMS BASED ON TRADITIONAL HOMEOPATHIC PRACTICE, NOT ACCEPTED MEDICAL EVIDENCE NOT FDA EVALUATED.
This product is not intended to diagnose, treat, cure, or prevent any disease.

Uses
Temporarily relieves occasional foamy urine, swelling in any area of the body, high blood pressure levels, elevated body temperature, rashes, and generalized aches.*

Uses
Temporarily relieves occasional foamy urine, swelling in any area of the body, high blood pressure levels, elevated body temperature, rashes, and generalized aches.*

Entire package label